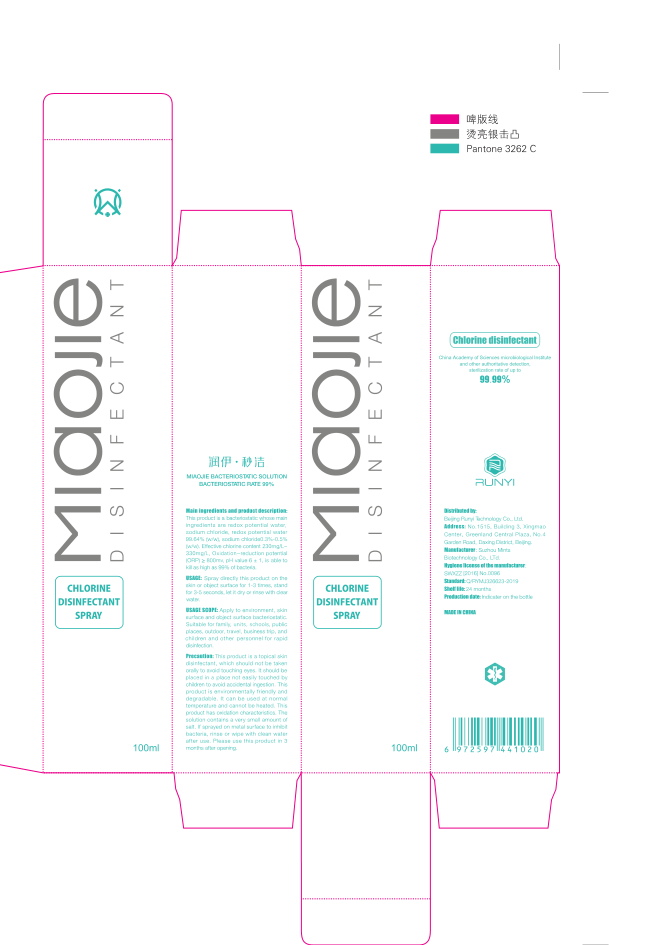 DRUG LABEL: RUNYI MIAOJIE Bacteriostatic solution
NDC: 96321-001 | Form: SPRAY
Manufacturer: Vincent International Distributing Inc
Category: otc | Type: HUMAN OTC DRUG LABEL
Date: 20200729

ACTIVE INGREDIENTS: HYPOCHLOROUS ACID 0.4 g/100 mL
INACTIVE INGREDIENTS: WATER

DOSAGE AND ADMINISTRATION

Store in a cool and dry place

INACTIVE INGREDIENT

Water

INDICATIONS AND USAGE

Spray directly this product on the skin or object surface for 1-3 times, stand for 3-5 seconds, let it dry or rinse with clear water.

ACTIVE INGREDIENT

Water

keep out of reach of children

PURPOSE

Disinfection
Sterilization

WARNINGS

This product is a topical skin disinfectant, which should not be taken orally to avoid touching eyes. It should be placed in a place not easily touched by children to avoid accidental ingestion. This product is environmentally friendly and degradable. It can be used at normal temperature and cannot be heated. This product has oxidation characteristics. The solution contains a very small amount of
salt. If sprayed on metal surface to inhibit bacteria, rinse or wipe with clean water after use. Please use this product in 3 months after opening.